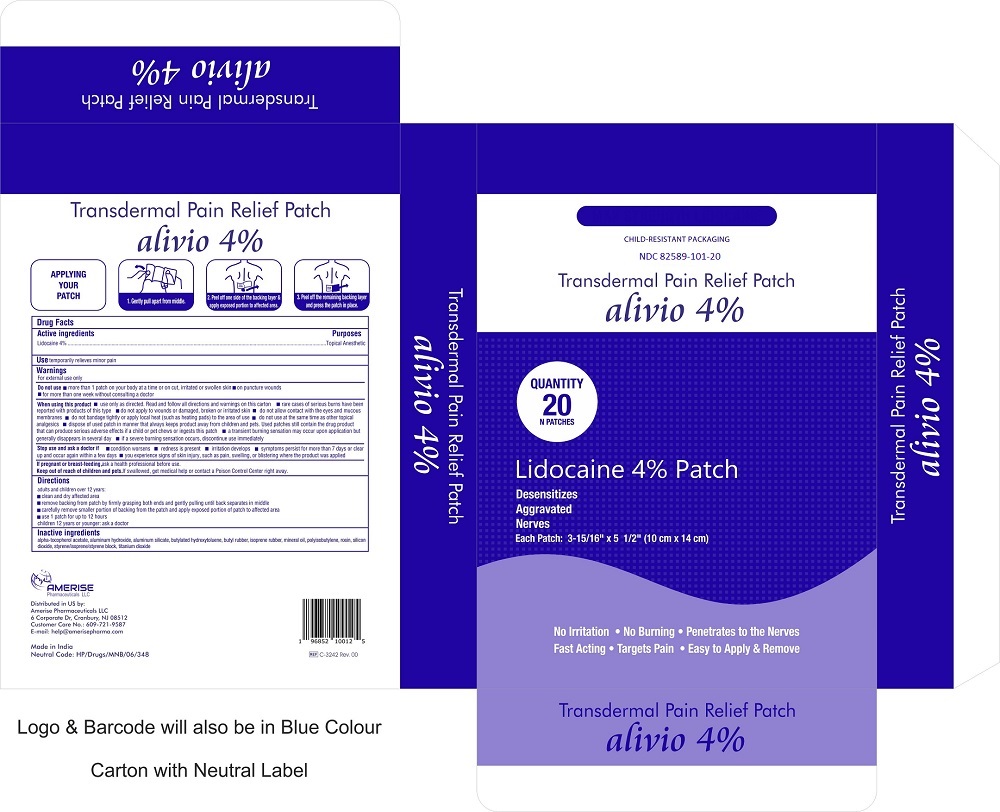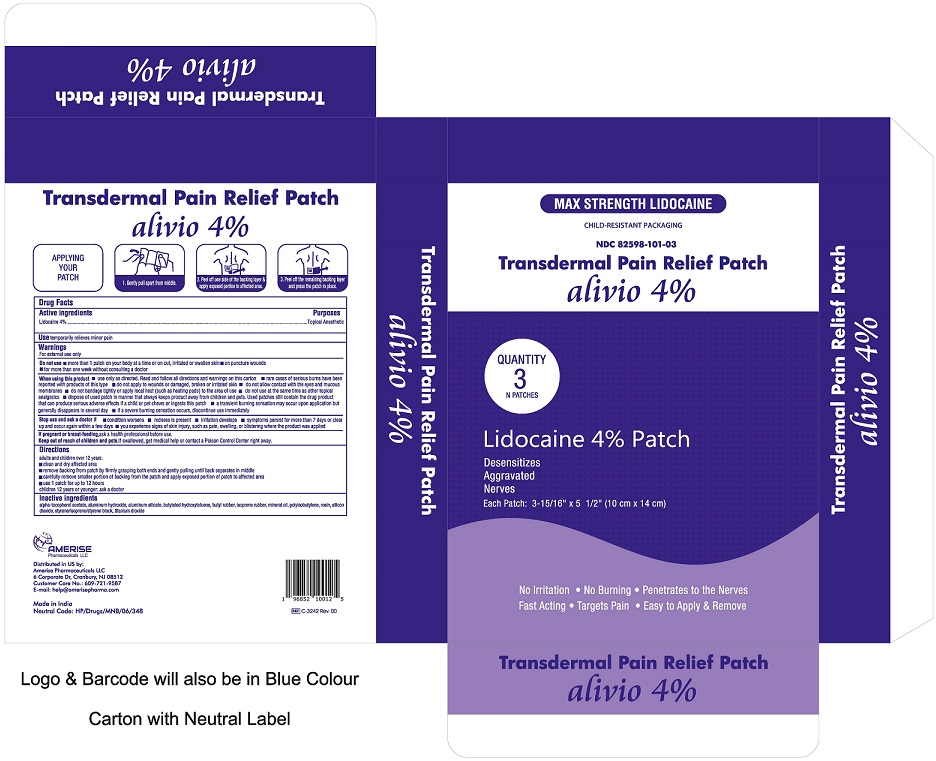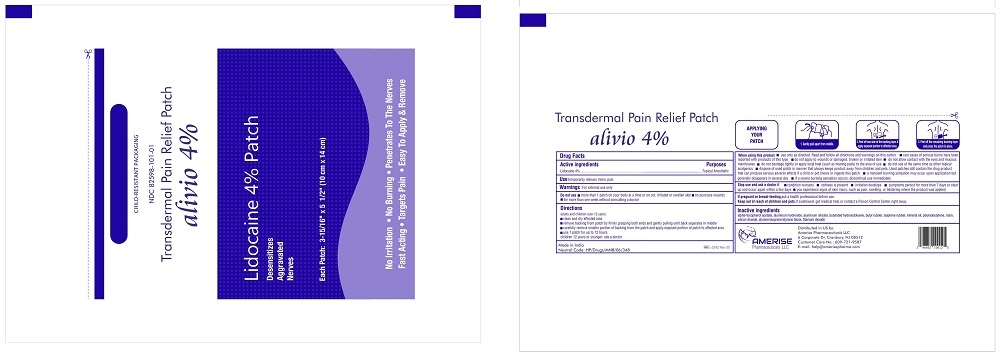 DRUG LABEL: Alivio
NDC: 82598-101 | Form: PATCH
Manufacturer: Amerise Pharmaceuticals LLC
Category: otc | Type: HUMAN OTC DRUG LABEL
Date: 20251023

ACTIVE INGREDIENTS: LIDOCAINE 4 g/1 1
INACTIVE INGREDIENTS: ALPHA-TOCOPHEROL ACETATE; ALUMINUM HYDROXIDE; ALUMINUM SILICATE; BUTYLATED HYDROXYTOLUENE; MINERAL OIL; ROSIN; SILICON DIOXIDE; STYRENE/ISOPRENE/STYRENE BLOCK COPOLYMER; TITANIUM DIOXIDE; ISOPRENE; ISOBUTYLENE; POLYISOBUTYLENE (1000 MW)

Alivio 4%
Lidocaine 4% Patch
Transdermal Pain Relief Patch

Active Ingredients

Lidocaine 4% .................................... Topical Anesthetic

Use

Temporarily relieves minor pain

PURPOSE

Temporarily relieves minor pain

Warnings

For external use only.

Do not use

- more than 1 patch on your body at a time or on cut, irritated or swollen skin
- on puncture wounds
- for more than one week without consulting a doctor

When using this product

- use only as directed. Read and follow all directions and warning on this carton
- rare cases of serious burns have been reported with products of this type
- do not apply to wonds or damaged, broken or irritated skin
- do not allow contact with the eyes and mucous membranes
- do not bandage tightly or apply local heat (such as heating pads) to the area of use
- do not use at the same time as other topical analgesics
- dispose of used patch in manner that always keep product away from children and pets. Used patches still contain the drug product that can produce serious adverse effects if a child or pet chews or ingests this patch
- a transient buring sensation may occur upon applicaiton but generally disappears in several day
- if a severe buring sensation occurs, discontinue use immediately

Stop use and ask a doctor if

- condition worsens
- redness is present
- irritation develops
- sypmtoms persist for more than 7 days or clear up and occur again within a few days
- you experience signs of skin injury, such as pain, swelling, or blistering where the product was applied.

If pregnant or breast-feeding, ask a health professional before use.

Keep out of reach of children and pets. If swallowed, get medical help or contact a Poison Control Center right away.

Directions

adults and children over 12 years:

- clean and dry affected area
- remove backing from patch by firmly grasping both ends and gently pulling until back separates in middle
- use 1 patch for up to 12 hours

Children 12 years or younger; ask a doctor

Inactive Ingredients

alpha-tocopherol acetate, aluminum hydroxide, aluminum silicate, butylated hydroxytoluene, butyl rubber, isoprene rubber, mineral oil, polyisobutylene, rosin, silicon dioxide, styrene/isoprene/styrene block, titanium dioxide

Distributed in US by:

Amerise Pharmaceuticals LLC

6 Corporate Dr, Cranbury, NJ 08512

Customer Care NO.: 609-721-9587

Email: help@amerisepharma.com